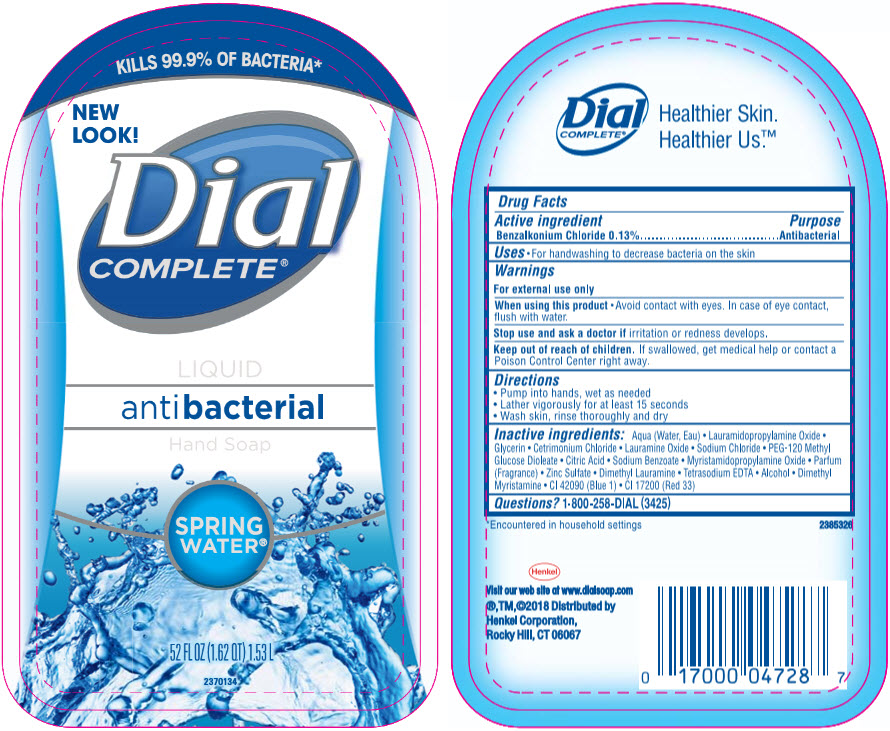 DRUG LABEL: Dial Complete Antibacterial Hand 
NDC: 69560-234 | Form: SOLUTION
Manufacturer: MID-CONTINENT PACKAGING, INC.
Category: otc | Type: HUMAN OTC DRUG LABEL
Date: 20210426

ACTIVE INGREDIENTS: Benzalkonium Chloride 1.3 mg/1 mL
INACTIVE INGREDIENTS: Water; Lauramidopropylamine Oxide; Lauramine Oxide; Cetrimonium Chloride; GLYCERIN; Sodium Chloride; PEG-120 METHYL GLUCOSE DIOLEATE; CITRIC ACID MONOHYDRATE; Sodium Benzoate; Edetate Sodium; Myristamidopropylamine Oxide; Zinc Sulfate Heptahydrate; Dimethyl Lauramine; Alcohol; Dimethyl Myristamine; FD&C BLUE NO. 1; D&C RED NO. 33

Dial Complete® Antibacterial Liquid Hand Soap
Spring Water®

Drug Facts

Active ingredient

Benzalkonium Chloride 0.13%

Purpose

Antibacterial

Uses

- For handwashing to decrease bacteria on the skin.

Warnings

For external use only

When using this product

- Avoid contact with eyes. In case of eye contact, flush with water.

Stop use and ask a doctor if irritation or redness develops.

Keep out of reach of children. If swallowed, get medical help or contact a Poison Control Center right away.

Directions

- Pump into hands, wet as needed
- Lather vigorously for at least 15 seconds
- Wash skin, rinse thoroughly and dry

Inactive ingredients

Aqua (Water, Eau) • Lauramidopropylamine Oxide • Glycerin • Cetrimonium Chloride • Lauramine Oxide • Sodium Chloride • PEG-120 Methyl Glucose Dioleate • Citric Acid • Sodium Benzoate • Myristamidopropylamine Oxide • Parfum (Fragrance) • Zinc Sulfate • Dimethyl Lauramine • Tetrasodium EDTA • Alcohol • Dimethyl Myristamine • CI 42090 (Blue 1) • CI 17200 (Red 33)

Questions?

1-800-258-DIAL (3425)

Distributed by
Henkel Corporation,
Rocky Hill, CT 06067

PRINCIPAL DISPLAY PANEL - 1.53 L Bottle Label

KILLS 99.9% OF BACTERIA*

NEW
LOOK!

Dial
COMPLETE®

LIQUID
antibacterial
Hand Soap

SPRING
WATER®

52 FL OZ (1.62 QT) 1.53 L

2370134